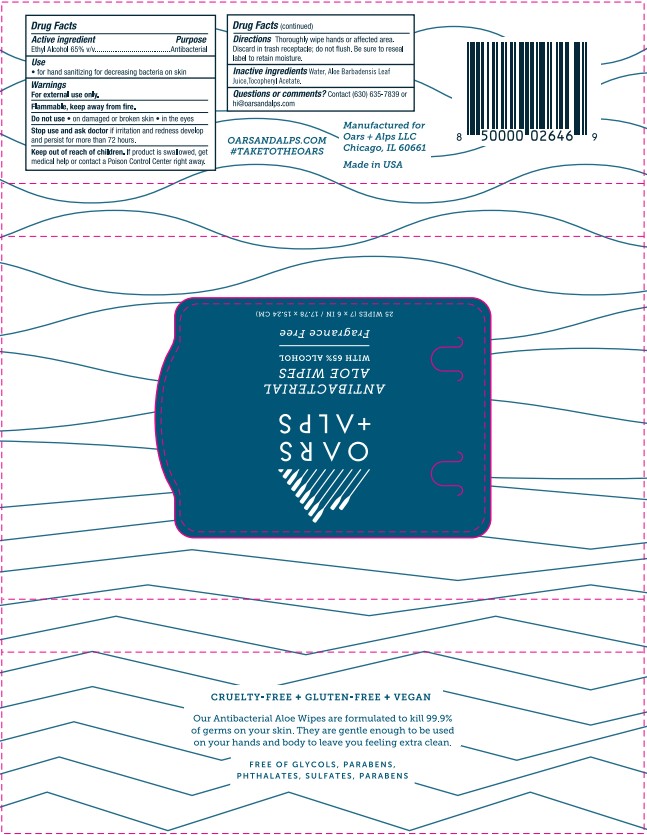 DRUG LABEL: Hand Sanitizing Wipe
NDC: 83046-101 | Form: CLOTH
Manufacturer: Oars And Alps LLC
Category: otc | Type: HUMAN OTC DRUG LABEL
Date: 20231206

ACTIVE INGREDIENTS: ALCOHOL 65 mL/100 mL
INACTIVE INGREDIENTS: .ALPHA.-TOCOPHEROL ACETATE; WATER; ALOE VERA LEAF

OARS+ALPS Antibacterial Aloe Wipes

Active Ingredeint

Ethyl Alcohol – 67% v/v

Purpose

Antibacterial

Use

- For hand sanitizing for decreasing bacteria on skin

Warnings

For external use only.

Flammable, keep away from fire.

Do not use • on damaged or broken skin • in the eyes

Stop use and ask doctor if irritation and redness develop and persist for more than 72 hours.

Keep out of reach of children

If product is swallowed, get medical help or contact a Poison Control Center right away.

Directions

Thoroughly wipe hands or affected area. Discard in trash receptacle; do not flush. Be sure to reseal label to retain moisture.

Inactive ingredients

Water, Aloe Barbadensis Leaf Juice, Tocopheryl Acetate.

Questions or comments?

Contact (630) 635-7839 or hi@oarsandalps.com

Label

OARS+ALPS

ANTIBACTERIAL

ALOE WIPES

WITH 65% ALCOHOL

Fragrance Free

25 WIPES (7 x 6 IN /17.78 x 15.24 CM)

CRUELTY FREE + GLUTEN FREE + VEGAN

Our Antibacterial Aloe Wipes are formulated to kill 99.9%

of germs on your skin. They are gentle enough to be used

on your hands and body to leave you feeling extra clean.

FREE OF GLYCOLS, PARABENS,

PHTHALATES, SULFATES

OARSANDALPS.COM

#TAKETOTHEOARS

Manufactured for

Oars + Alps LLC, Chicago, IL 60661

Made in USA

8 5000 02646 9